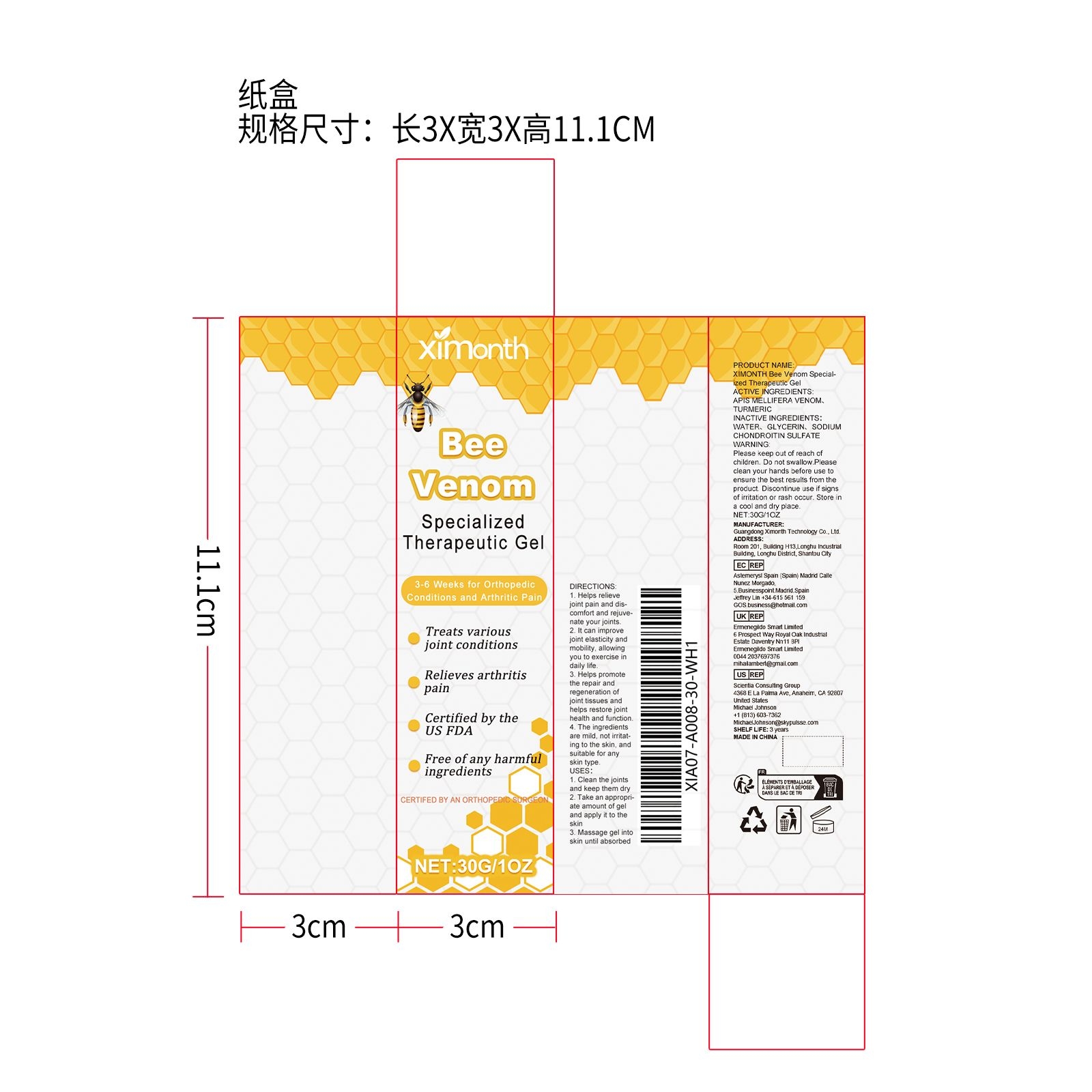 DRUG LABEL: XIMONTH Bee Venom Specialized Therapeutic Gel
NDC: 84660-045 | Form: GEL
Manufacturer: Guangdong Ximonth Technology Co., Ltd.
Category: otc | Type: HUMAN OTC DRUG LABEL
Date: 20241017

ACTIVE INGREDIENTS: APIS MELLIFERA VENOM 3 g/30 g; TURMERIC 9 g/30 g
INACTIVE INGREDIENTS: SODIUM CHONDROITIN SULFATE (PORCINE; 5500 MW) 4.5 g/30 g; GLYCERIN 4.5 g/30 g; WATER 9 g/30 g

Active Ingredient(s)

APIS MELLIFERA VENOM、TURMERIC

Purpose

1. Helps relieve joint pain and discomfort and rejuvenate your joints.
2. It can improve joint elasticity and mobility, allowing you to exercise in daily life.
3. Helps promote the repair and regeneration of joint tissues and helps restore joint health and function.
4. The ingredients are mild, not irritating to the skin, and suitable for any skin type.

Use

1.Clean the joints and keep them dry
2. Take an appropriate amount of gel and apply it to the skin
3. Massage gel into skin until absorbed

Warnings

Please keep out of reach of children. Do not swallow.Please clean your hands before use to ensure the best results from the product. Discontinue use if signs of irritation or rash occur. Store in a cool and dry place.

Do not use

Discontinue use if signs of irritation or rash occur.

Stop Use

Discontinue use if signs of irritation or rash occur.

KEEP OUT OF REACH OF CHILDREN

Please keep out of reach of children. Do not swallow.

STORAGE AND HANDLING

Store in a cool and dry place.

INACTIVE INGREDIENT

WATER、GLYCERIN、SODIUM CHONDROITIN SULFATE